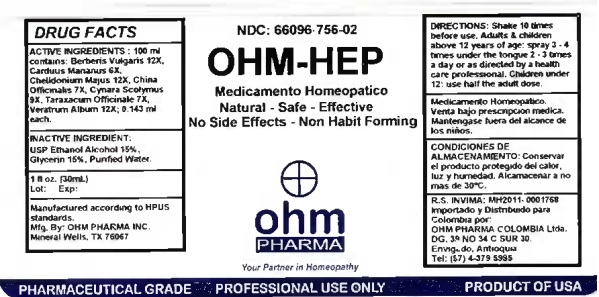 DRUG LABEL: OHM-HEP
NDC: 66096-756 | Form: SPRAY
Manufacturer: OHM PHARMA INC.
Category: homeopathic | Type: HUMAN OTC DRUG LABEL
Date: 20210111

ACTIVE INGREDIENTS: BERBERIS VULGARIS ROOT BARK 12 [hp_X]/30 mL; MILK THISTLE 6 [hp_X]/30 mL; CHELIDONIUM MAJUS 12 [hp_X]/30 mL; CINCHONA OFFICINALIS BARK 7 [hp_X]/30 mL; CYNARA SCOLYMUS LEAF 9 [hp_X]/30 mL; TARAXACUM OFFICINALE 7 [hp_X]/30 mL; VERATRUM ALBUM ROOT 12 [hp_X]/30 mL
INACTIVE INGREDIENTS: GLYCERIN; ALCOHOL; WATER

OHM-HEP

ACTIVE INGREDIENT

ACTIVE INGREDIENTS: 100 ml contains: Berberis Vulgaris 12X, Carduus Marianus 6X, Chelidonium Majus 12X, China Officinalis 7X, Cynara Scolymus 9X, Taraxacum Officinale 7X, Veratrum Album 12X; 0.143 ml each.

INDICATIONS AND USAGE

USES: Temporarily relieves primary and secondary functional hepatic disorders.**

WARNINGS

Medicamento Homeopatico.

Venta bajo prescripcion medica.

Mantengase fuera del alcance de niños.

KEEP OUT OF REACH OF CHILDREN

Mantengase fuera del alcance de niños.

DOSAGE AND ADMINISTRATION

DIRECTIONS: Shake 10 times before use. Adults & children above 12 years of age: spray 3 - 4 times a day or as directed by a health care professional. Children under 12: use half the adult dose.

OTHER SAFETY INFORMATION

CONDICIONES DE ALMACENAMIENTO: Conservar el producto protegido del calor, luz y humedad. Alcamacenar a no mas de 30°C.

INACTIVE INGREDIENT:

USP Ethanol Alcohol 15%, Glycerin 15%, Purified Water.

QUESTIONS

Manufactured according to HPUS standards.

Mfg. By: OHM PHARMA INC.

Mineral Wells, Tx 76067

R.S. INVIMA: MH2011-0001768

Importado y Distribuido para

Colombia por:

OHM PHARMA COLOMBIA Ltda.

DG. 39 NO 34 C SUR 30.

Enviado, Antioquia

Tel: (57) 4-379 5995

PACKAGE LABEL

NDC: 66096-756-02

OHM-HEP

Medicamento Homeopatico

Natural - Safe - Effective

No Side Effects - Non Habit Forming

ohm PHARMA

PURPOSE

USES: Temporarily relieves primary and secondary functional hepatic disorders.**